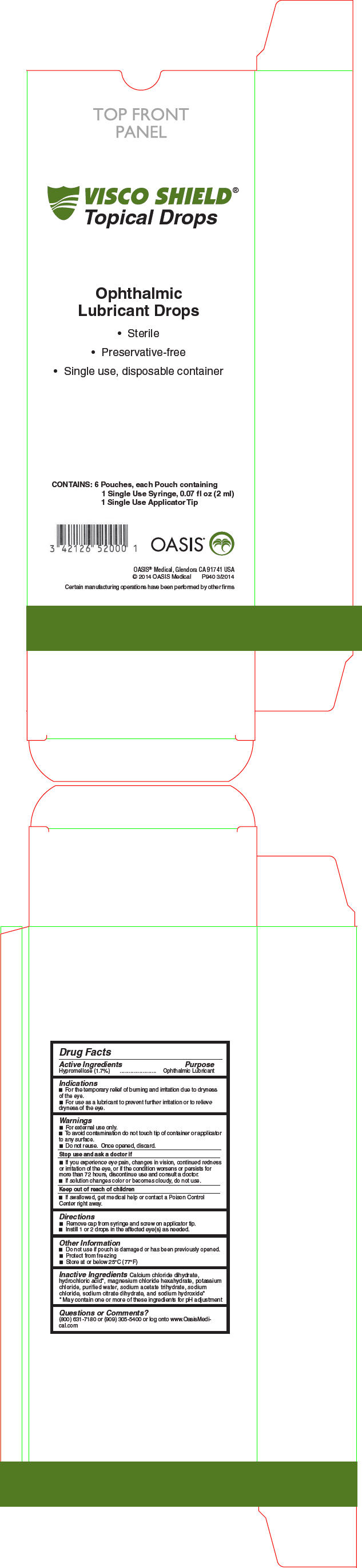 DRUG LABEL: VISCO SHIELD
NDC: 42126-5200 | Form: SOLUTION/ DROPS
Manufacturer: OASIS Medical, Inc.
Category: otc | Type: HUMAN OTC DRUG LABEL
Date: 20250122

ACTIVE INGREDIENTS: HYPROMELLOSE 2208 (15000 MPA.S) 17 mg/1 mL
INACTIVE INGREDIENTS: CALCIUM CHLORIDE; MAGNESIUM CHLORIDE; HYDROCHLORIC ACID; POTASSIUM CHLORIDE; SODIUM ACETATE; SODIUM CHLORIDE; SODIUM CITRATE, UNSPECIFIED FORM; SODIUM HYDROXIDE; WATER

VISCO SHIELD®
Ophthalmic Lubricant Drops

Drug Facts

Active Ingredients

Hypromellose (1.7%)

Purpose

Ophthalmic lubricant

Uses

- For the temporary relief of burning and irritation due to dryness of the eye
- For use as a lubricant to prevent further irritation or to relieve dryness of the eye

Warnings

- For external use only
- To avoid contamination do not touch tip of container or applicator to any surface
- Once opened, discard
- Do not reuse

Stop use and ask a doctor if

- You experience eye pain, changes in vision, continued redness or irritation of the eye, or if the condition worsens or persists for more than 72 hours, discontinue use and consult a doctor
- If solution changes color or becomes cloudy, do not use

Keep out of reach of children. If swallowed, get medical help or contact a Poison Control Center right away.

Directions

- Remove cap from syringe and screw on applicator tip
- Instill 1 or 2 drops in the affected eye(s) as needed.

Questions, or comments

(800) 631-7180 or (909) 305-5400 or log onto www.oasistears.com

Other information

- Do not sue if pouch is damage or has been previously opened
- Protect from freezing
- Store at or below 77°F/25°C

Inactive Ingredients

Calcium chloride dihydrate, hydrochloric acid [May contain one or more of these ingredients for pH adjustment] , magnesium chloride hexahydrate, potassium chloride, purified water, sodium acetate trihydrate, sodium chloride, sodium citrate dihydrate, and sodium hydroxide

PRINCIPAL DISPLAY PANEL - 2 ml Syringe Carton

VISCO SHIELD®
Topical Drops

Ophthalmic
Lubricant Drops

- Sterile
- Preservative-free
- Single use, disposable container

CONTAINS: 6 Pouches, each Pouch containing
1 Single Use Syringe, 0.07 fl oz (2 ml)
1 Single Use Applicator Tip

OASIS®

OASIS® Medical, Glendora CA 91741 USA
© 2014 OASIS Medical
P940 3/2014

Certain manufacturing operations have been performed by other firms